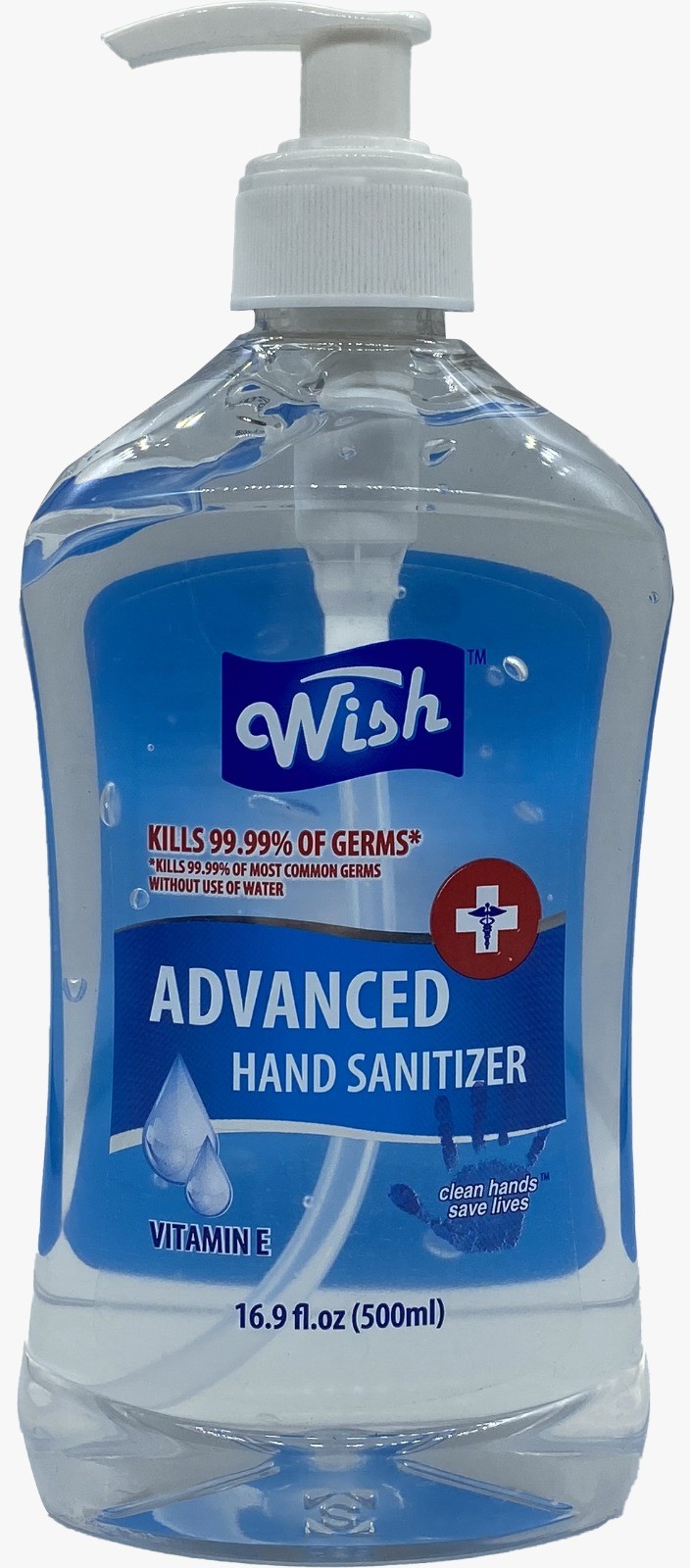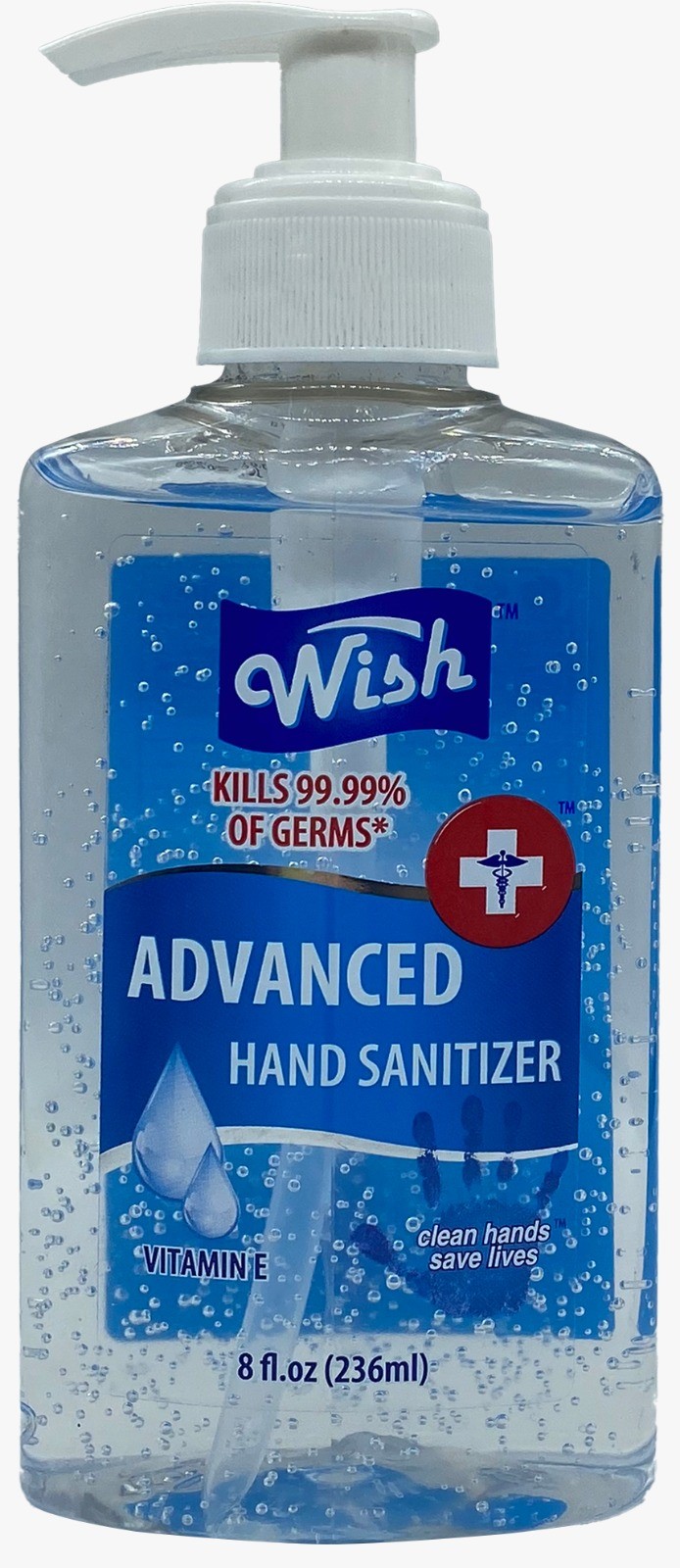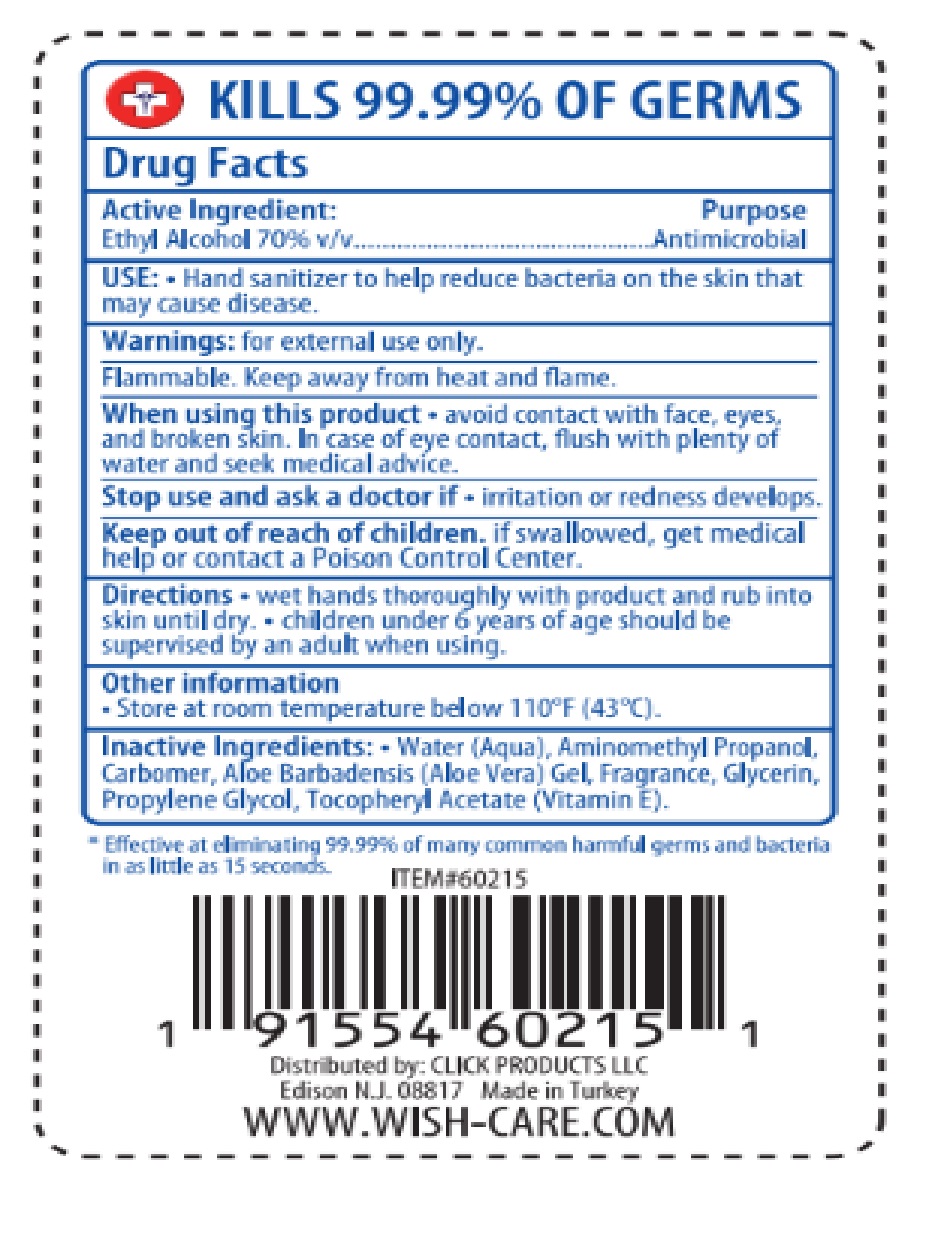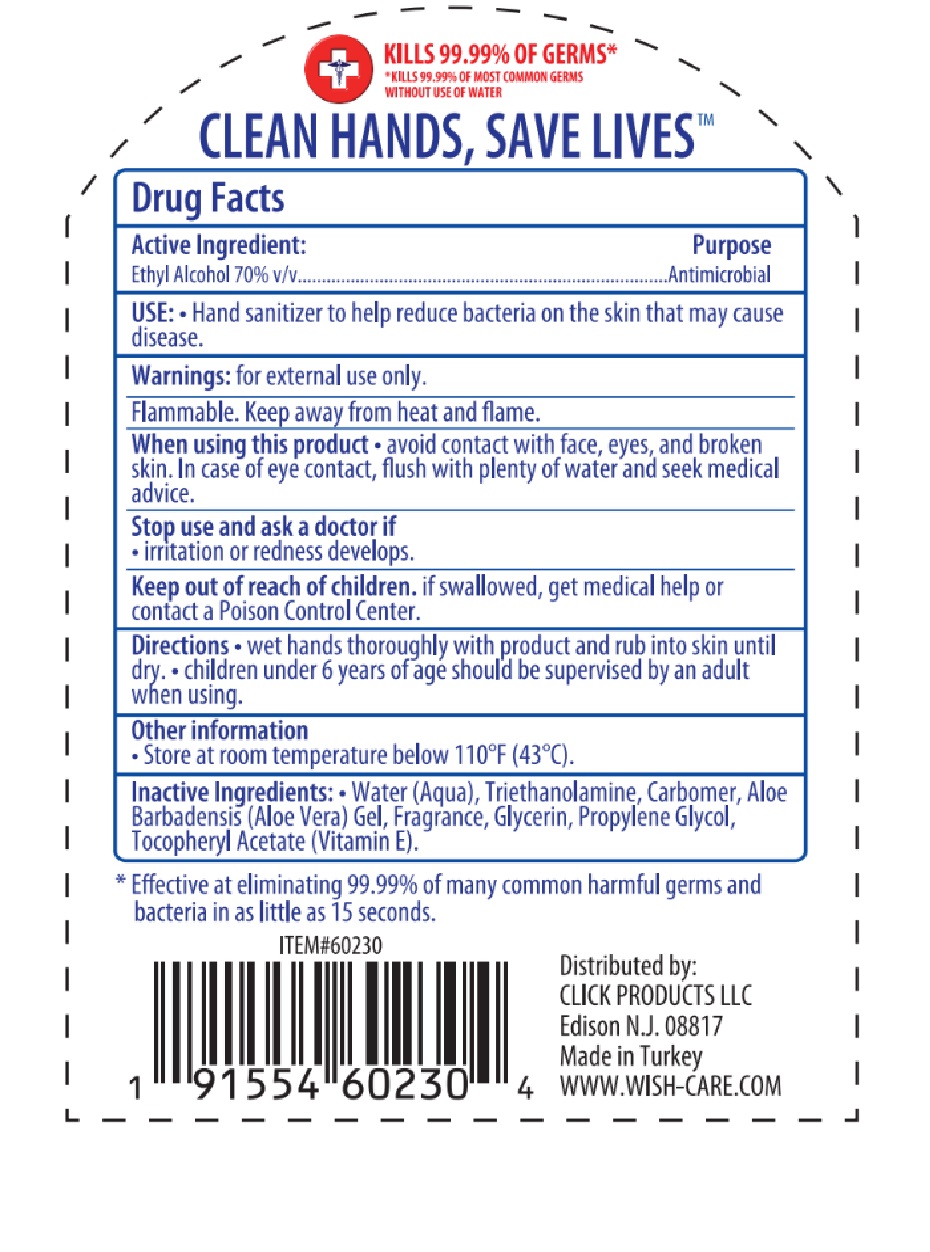 DRUG LABEL: WISH HAND SANITIZER
NDC: 76567-0230 | Form: GEL
Manufacturer: TSM BRANDS LLC
Category: otc | Type: HUMAN OTC DRUG LABEL
Date: 20240829

ACTIVE INGREDIENTS: ALCOHOL 70 mL/100 mL
INACTIVE INGREDIENTS: WATER 29.43 mL/100 mL; PROPYLENE GLYCOL 0.1 mL/100 mL; .ALPHA.-TOCOPHEROL ACETATE 0.01 mL/100 mL; GLYCERIN 0.1 mL/100 mL; CARBOMER HOMOPOLYMER, UNSPECIFIED TYPE 0.28 mL/100 mL; TROLAMINE 0.07 mL/100 mL; ALOE VERA LEAF 0.01 mL/100 mL

WISH HAND SANITIZERS

Front Labels

WISH HS 500ml front.jpg

Wish HS.jpg

Back Label

Drug Facts

Active Ingreditents Purpose

Ethyl Alcohol 70% V/V Antimicrobial

Use

Hand sanitizer to help reduce bacteria on the skin that may cause disease

Warnings

For external use only

Flammable

Keep away from heat and flame

When using this product

Avoid contact with face, eyes and broken skin

In case of eye contact

Flush with plenty of water and seek medical advise

Stop use and ask for a doctor if

Irritation or redness develops

Keep out of reach of children

If swallowed, get medical help or contact a posion control center

Directions

Wet hands thoroughly with product and rub into skin until dry

Children under 6 years of age should be supervised by an adult when using

Other information

Store at room temperature below 100 F (43 C)

Inactive ingredients

Water (aqua), aminomethyl propanol. carbomer, aloe barbadensis (aloe vera) gel, fragrance, glyserin, propylen glycol, tocopheryl acetate (vitamin E)

Wsh HS 236ml back.jpg

Wish HS back 500ml.jpg

Active Ingredient Purpose

Ethyl Alcohol 70% V/V Antimicrobial

Wish HS 236ml back.jpg

Wish HS back 500ml.jpg

Keep out of reach of children

If swallowed, get medical help or contanct a Poison Control Center

Wish HS 236ml back.jpg

Wish HS back 500ml.jpg

Stop use and Ask a Doctor If

irritation or redness develops

Wish HS 236ml back.jpg

Wish HS back 500ml.jpg

Purpose

Antimicrobial

Wish HS 236ml back.jpg

Wish HS back 500ml.jpg

Warnings

For external use only

Flammable

Keep away from heat and flame.

Wish HS 236ml back.jpg

Wish HS back 500ml.jpg

When using this product

Avoid contact with face, eyes and broken skin. In case of eye contact, flush with plenty of water and seek medical advice

Wish HS 236ml back.jpg

Wish HS back 500ml.jpg

Directions

Wet hands thoroughly with product and rub into skin until dry. Children under 6 years of age should be supervised by an adult when using

Inactive Ingredients

Water (aqua), aminomethyl propanol, carbomer, aloe barbadensis (aloe vera) gel, fragrance, glycerin, propylen glycol, tocopheryl acetate (vitamine e)

Use

Use hand sanitizer to help reduce bacteria on the skin that may cause a disease.